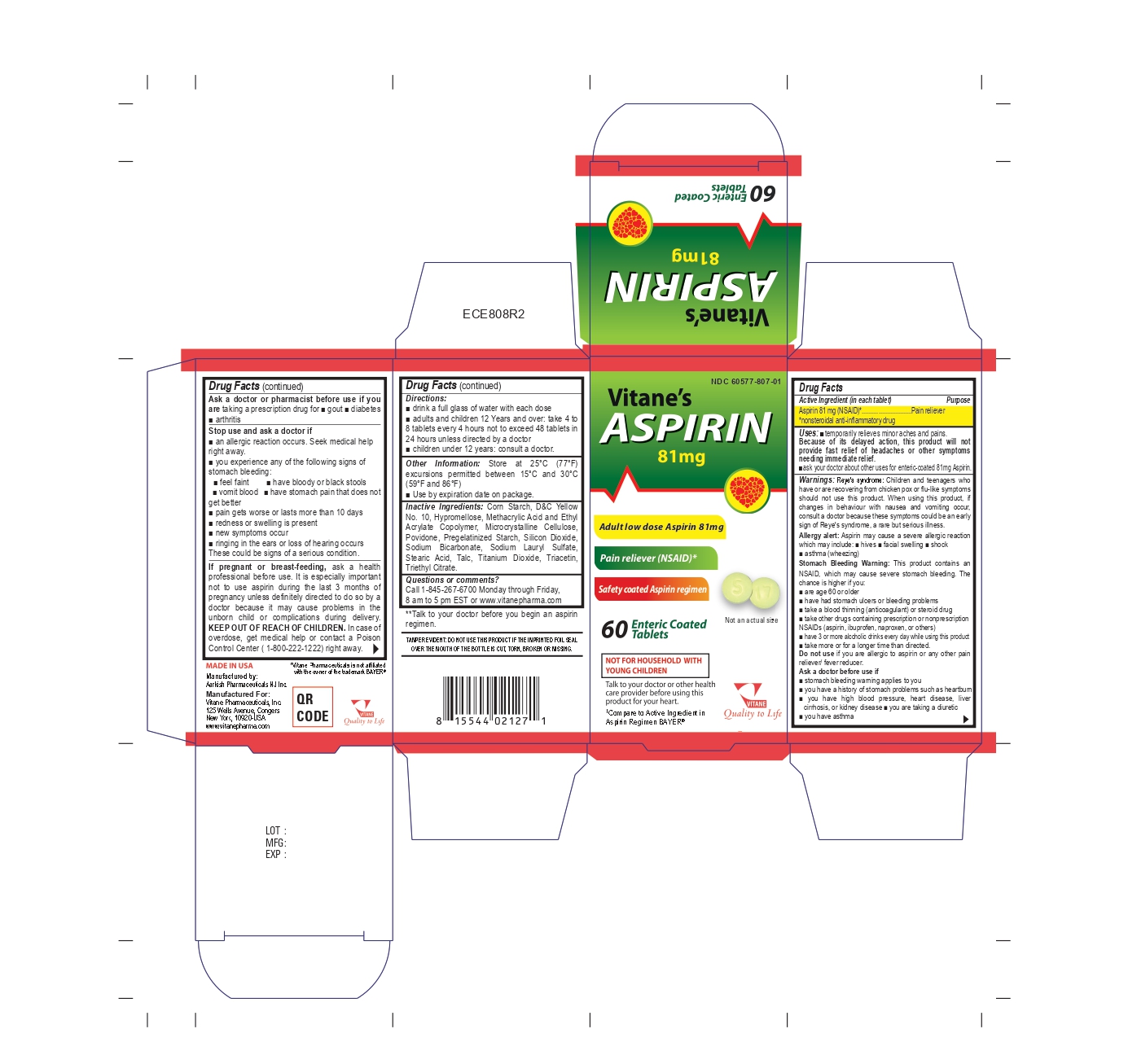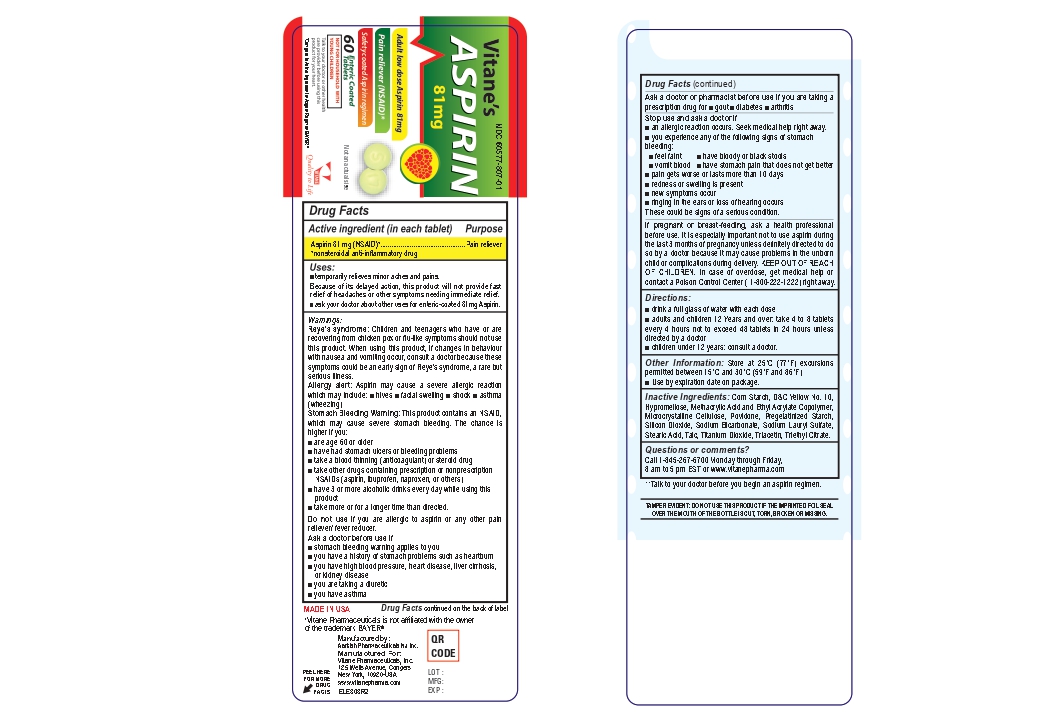 DRUG LABEL: Aspirin 81mg
NDC: 60577-807 | Form: TABLET
Manufacturer: VITANE PHARMACEUTICALS, INC
Category: otc | Type: HUMAN OTC DRUG LABEL
Date: 20251015

ACTIVE INGREDIENTS: ASPIRIN 81 mg/1 1
INACTIVE INGREDIENTS: STARCH, CORN; STEARIC ACID; TALC; SODIUM LAURYL SULFATE; TITANIUM DIOXIDE; TRIETHYL CITRATE; TRIACETIN; METHACRYLIC ACID AND ETHYL ACRYLATE COPOLYMER; HYPROMELLOSE, UNSPECIFIED; CELLULOSE, MICROCRYSTALLINE; D&C YELLOW NO. 10; POVIDONE; SODIUM BICARBONATE; SILICON DIOXIDE

ACTIVE INGREDIENT

Aspirin 81 mg (NSAID*)

*nonsteroidal anti-inflamatory drug

PURPOSE

Pain reliever

USES

- temporarily relieves minor aches and pains.

Because of its delayed action, this product will not provide fast relief of headaches or other symptoms needing immediate relief.

- ask your doctor about other uses for enteric-coated 81 mg Aspirin.

INACTIVE INGREDIENT

corn starch, pregelatinized starch, povidone, microcrystalline celulose, colloidal silicon dioxide, stearic acid, methacrylic acid and ethyl acrylate copolymer, talc, titanium dioxide, triethyl citrate, sodium bicarbonate, sodium lauryl sulfate, d&c yellow #10, hypromellose, triacetin.

WARNINGS

Reye’s syndrome: Children and teenagers who have or are recovering from chicken pox or flu-like symptoms should not use this product. When using this product, if changes in behavior with nausea and vomiting occur, consult a doctor because these symptoms could be an early sign of Reye’s syndrome, a rare but serious illness.

ALLERGY ALERT

Aspirin may cause a severe allergic reaction which may include:

- hives

- facial swelling

- shock

- asthma (wheezing)

Stomach bleeding warning: This product contains an NSAID, which may cause severe stomach bleeding. The chance is higher if you:

- are age 60 or older

- have had stomach ulcers or bleeding problems

- take a blood thinning (anticoagulant) or steroid drug

- take other drugs containing prescription or nonprescription NSAIDs (aspirin, ibuprofen, naproxen, or others)

- have 3 or more alcoholic drinks every day while using this product

- take more or for a longer time than directed

DO NOT USE SECTION

Stop use and ask a doctor if

- an allergic reaction occurs. Seek medical help right away

- you experience any of the following signs of stomach bleeding: feel faint, have bloody or black stools, vomit blood, have stomach pain that does not get better

- pain gets worse or lasts more than 10 days

- redness or swelling is present

- new symptoms occur

- ringing in the ears or loss of hearing occurs

these could be signs of a serious condition.

ASK DOCTOR/PHARMACIST SECTION

Ask a doctor or pharmacist before use if you are

- taking a prescription drug for gout, diabetes, or arthritis

- taking any other medication

- under a doctor’s care for any serious condition

STOP USE SECTION

Stop use and ask a doctor if

- an allergic reaction occurs. Seek medical help right away

- you experience any of the following signs of stomach bleeding: feel faint, have bloody or black stools, vomit blood, have stomach pain that does not get better

- pain gets worse or lasts more than 10 days

- redness or swelling is present

- new symptoms occur

- ringing in the ears or loss of hearing occurs

these could be signs of a serious condition.

PREGNANCY OR BREAST FEEDING SECTION

If pregnant or breast-feeding, ask a health professional before use. It is especially important not to use aspirin during the last 3 months of pregnancy unless definitely directed to do so by a doctor because it may cause problems in the unborn child or complications during delivery.

Ask a doctor before use if

stomach bleeding warning applies to you

- you have a history of stomach problems such as heartburn
- you have high blood pressure, heart disease, liver cirrhosis, or kidney disease
- you are taking a diuretic
- you have asthma

KEEP OUT OF REACH OF CHILDREN SECTION

Keep out of reach of children. In case of overdose, get medical help or contact a Poison Control Center right away (1-800-222-1222).

STORAGE

- store at 25°C (77°F); excursions permitted between 15°and 30°C (59°and 86°F)
- -use by expiration date on package.

DIRECTIONS

- drink a full glass of water with each dose
- adults and children 12 years and over: Take 4 to 8 tablets every 4 hours, not to exceed 48 tablets in 24 hours unless directed by a doctor
- children under 12 years: Consult a doctor

PRINCIPAL DISPLAY PANEL

NDC 60577-807-01

Vitane's

Aspirin 81mg

Pain Reliever -

Aspirin USP 81 mg (NSAID) Enteric Coated

60 tablets